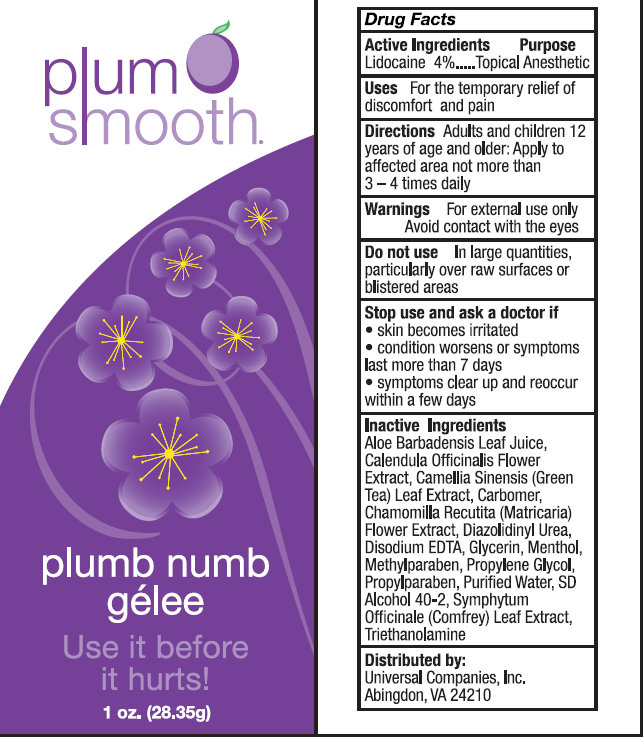 DRUG LABEL: Plum Smooth Plumb Numb Gelee
NDC: 49911-884 | Form: GEL
Manufacturer: Universal Companies, Inc.
Category: otc | Type: HUMAN OTC DRUG LABEL
Date: 20231109

ACTIVE INGREDIENTS: LIDOCAINE 4 g/100 g
INACTIVE INGREDIENTS: ALOE VERA LEAF; CALENDULA OFFICINALIS FLOWER; CAMELLIA SINENSIS FLOWER; MATRICARIA CHAMOMILLA WHOLE; DIAZOLIDINYL UREA; EDETATE DISODIUM; GLYCERIN; MENTHOL; METHYLPARABEN; PROPYLENE GLYCOL; PROPYLPARABEN; WATER; ALCOHOL; COMFREY LEAF; TROLAMINE

Active Ingredients

Lidocaine 4%

Purpose

Topical Anesthetic

Uses

For the temporary relief of discomfort and pain

Directions

Adults and children 12 years of age and older: Apply to affected area not more than 3-4 times daily

Warnings

For external use only

Avoid contact with eyes

Do not use

In large quantities, particularly over raw surfaces or blistered areas

STOP USE

- skin becomes irritated
- condition worsens or symptoms last more than 7 days
- symptoms clear up and reoccur within a few days

Inactive Ingredients

Aloe Barbadensis Leaf Juice, Calendula Officinalis Flower Extract, Camellia Sinensis (Green Tea) Leaf Extract, Carbomer, Chamomilla Recutita (Matricaria) Flower Extract, Diazolidinyl Urea, Disodium EDTA, Glycerin, Menthol, Methylparaben, Propylene Glycol, Propylparaben, Purified Water, SD Alcohol 40-2, Symphytum Officinale (Comfrey) Leaf Extract, Triethanolamine

Distributed by:

Universal Companies, Inc. Abingdon, VA 24210